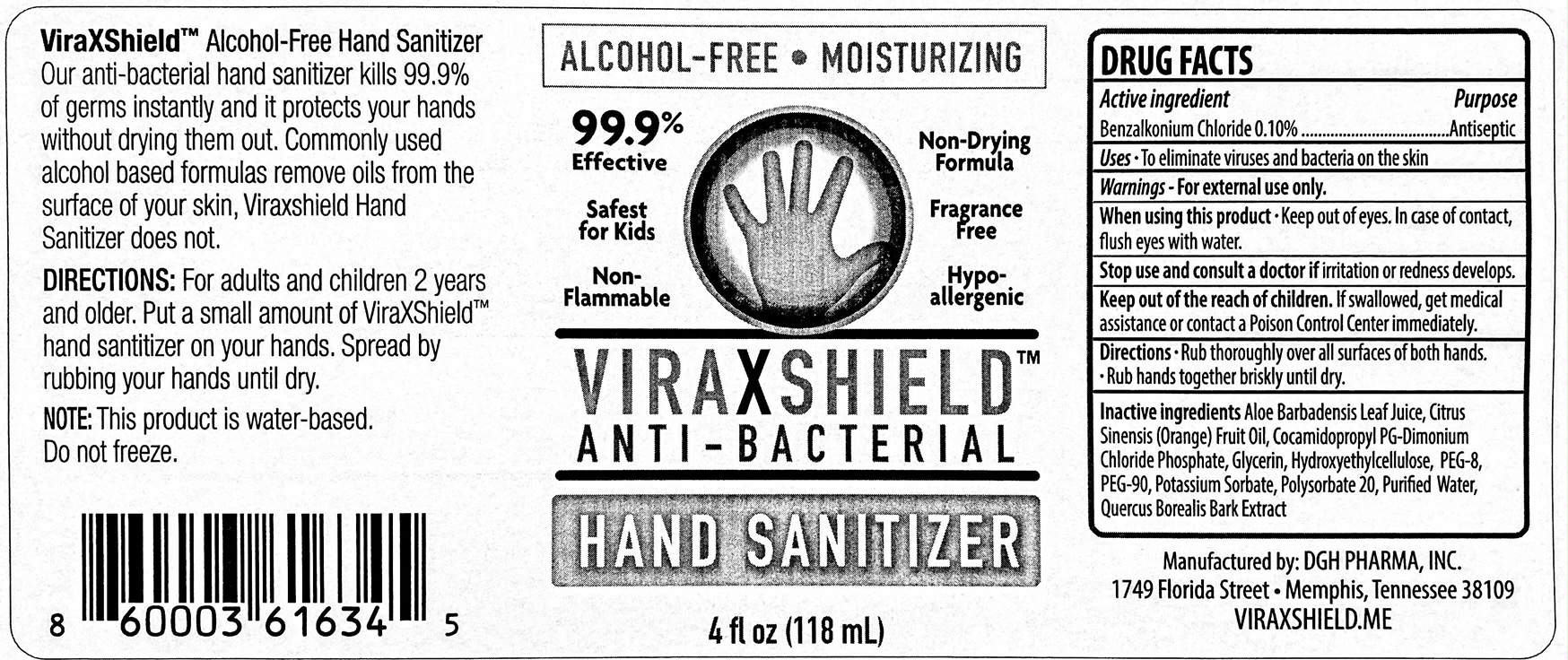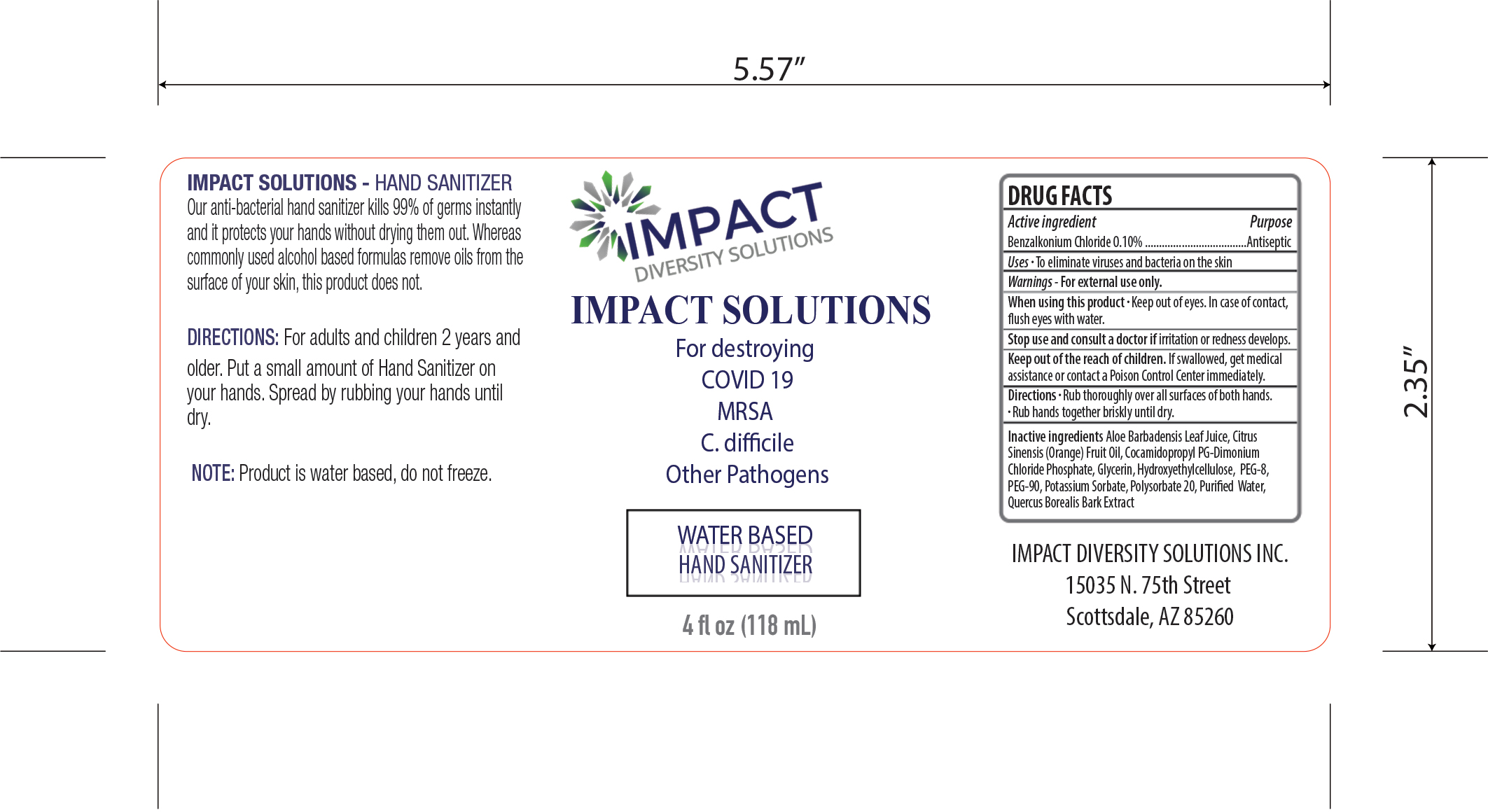 DRUG LABEL: Hand Sanitizer
NDC: 77238-221 | Form: GEL
Manufacturer: DGH Pharma, Inc.
Category: otc | Type: HUMAN OTC DRUG LABEL
Date: 20201009

ACTIVE INGREDIENTS: BENZALKONIUM CHLORIDE 0.1 g/100 mL
INACTIVE INGREDIENTS: POLYETHYLENE GLYCOL 4000 2.2 g/100 mL; POLYETHYLENE GLYCOL 400 1.8 g/100 mL; WATER; QUERCUS RUBRA BARK 1 g/100 mL; POLYSORBATE 20 0.2 g/100 mL; COCAMIDOPROPYL PG-DIMONIUM CHLORIDE PHOSPHATE 1 g/100 mL; ALOE VERA LEAF 1 g/100 mL; HYDROXYETHYL CELLULOSE, UNSPECIFIED 0.7 g/100 mL; ORANGE OIL 0.1 g/100 mL; POTASSIUM SORBATE 0.05 g/100 mL

Hand Sanitizer

Active Ingredient(s)

Benzalkonium Chloride 0.10% w/w. Purpose: Antiseptic

Purpose

Antiseptic, Hand Sanitizer

Use

To eliminate viruses and bacteria on the skin

Warnings

For external use only.

When using this product keep out of eyes. In case of contact, flush eyes with water.
Stop use and ask a doctor if irritation or redness develops
Keep out of reach of children. If swallowed, get medical assistance or contact a Poison Control Center immediately.

Stop use and ask a doctor if irritation or redness develops.

Keep out of reach of children. If swallowed, get medical assistance or contact a Poison Control Center immediately.

Directions

- Rub thoroughly over all surfaces of both hands.
- Rub hands toghether briskly unitl dry.

Inactive ingredients

Aloe Barbadensis Leaf Juice, Citrus Sinensis (Orange) Fruit Oil, Cocamidopropyl PG-Dimonium Chloride Phosphate, Glycerin, Hydroxyethylcellulose, PEG-8, PEG-90, Potassium Sorbate, Polysorbate 20, Purified Water, Quercus Borealis Bark Extract